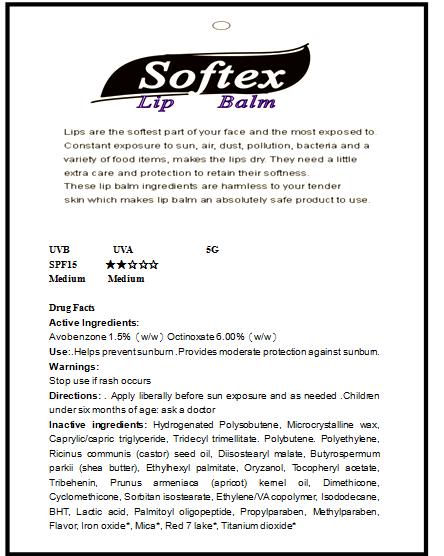 DRUG LABEL: LIP BALM
NDC: 51414-300 | Form: OINTMENT
Manufacturer: Yuyao Jessie Commodity Co., Ltd.
Category: otc | Type: HUMAN OTC DRUG LABEL
Date: 20220701

ACTIVE INGREDIENTS: AVOBENZONE 1.5 g/100 g; OCTINOXATE 6 g/100 g
INACTIVE INGREDIENTS: CELLULOSE, MICROCRYSTALLINE; MEDIUM-CHAIN TRIGLYCERIDES; POLYETHYLENE GLYCOL; RICINUS COMMUNIS SEED; SHEA BUTTER; ETHYLHEXYL PALMITATE; GAMMA ORYZANOL; .ALPHA.-TOCOPHEROL ACETATE, DL-; TRIBEHENIN; APRICOT SEED OIL; DIMETHICONE; CYCLOMETHICONE; PEG-40 SORBITAN DIISOSTEARATE; ETHYLENE-VINYL ACETATE COPOLYMER (15% VINYL ACETATE); ISODODECANE; BUTYLATED HYDROXYTOLUENE; LACTIC ACID; PROPYLPARABEN; METHYLPARABEN; FERRIC OXIDE RED; MICA; D&C RED NO. 7; TITANIUM DIOXIDE

51414-300

Lip Balm

Lips are the softest part of your face and the most exposed to Constant exposure to sun,air,dust,pollution,bacteria and a variety of food items,makes the lips dry,They need a little extra care and protection to retain their softness.These lip balm ingredients are harmless to your tender skin which makes lip balm an absolutely safe product to use
UVB UVA 5G
SPF15 ★★☆☆☆
Medium Medium

Active Ingredients:

Avobenzone 1.5%（w/w）Octinoxate 6.00%（w/w）

USE

Helps prevent sunburn .Provides moderate protection against sunburn.

Warnings:

Stop use if rash occurs

Directions:

Apply liberally before sun exposure and as needed .Children under six months of age: ask a doctor

Inactive ingredients

Hydrogenated Polysobutene, Microcrystalline wax, Caprylic/capric triglyceride, Tridecyl trimellitate. Polybutene. Polyethylene, Ricinus communis (castor) seed oil, Diisostearyl malate, Butyrospermum parkii (shea butter), Ethylhexyl palmitate, Oryzanol, Tocopheryl acetate, Tribehenin, Prunus armeniaca (apricot) kernel oil, Dimethicone, Cyclomethicone, Sorbitan isostearate, Ethylene/VA copolymer, Isododecane, BHT, Lactic acid, Palmitoyl oligopeptide, Propylparaben, Methylparaben, Flavor, Iron oxide*, Mica*, Red 7 lake*, Titanium dioxide*